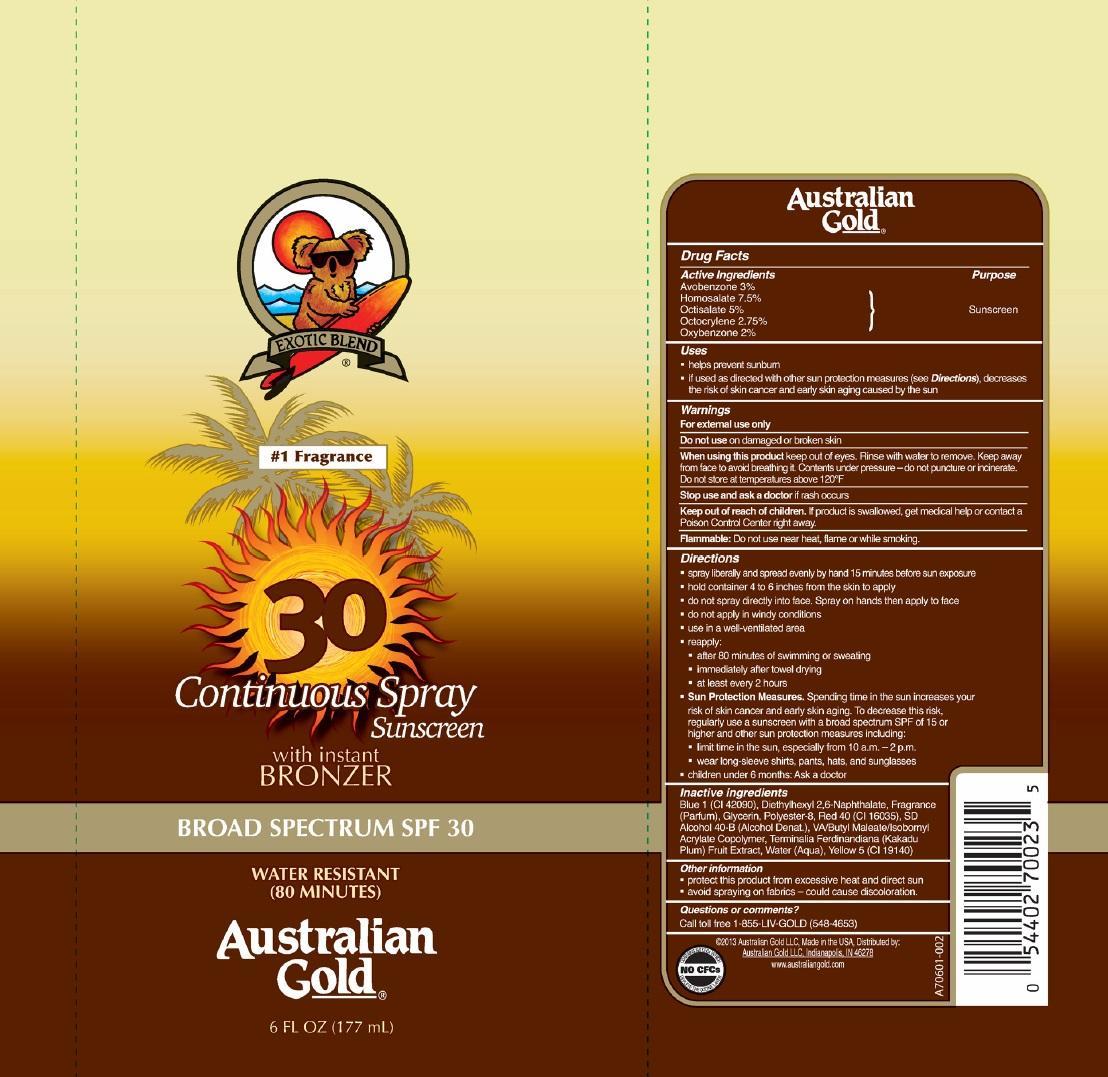 DRUG LABEL: Australian Gold
NDC: 58443-0071 | Form: LOTION
Manufacturer: Prime Enterprises, Inc.
Category: otc | Type: HUMAN OTC DRUG LABEL
Date: 20200117

ACTIVE INGREDIENTS: AVOBENZONE 25.1 mg/1 mL; HOMOSALATE 62.7 mg/1 mL; OCTISALATE 41.8 mg/1 mL; OCTOCRYLENE 22.9 mg/1 mL; OXYBENZONE 16.7 mg/1 mL
INACTIVE INGREDIENTS: CARBOMER COPOLYMER TYPE A (ALLYL PENTAERYTHRITOL CROSSLINKED); FD&C BLUE NO. 1; POLYESTER-8 (1400 MW, CYANODIPHENYLPROPENOYL CAPPED); ALCOHOL; FD&C RED NO. 40; DIBUTYL MALEATE; WATER; GLYCERIN; KAKADU PLUM; FD&C YELLOW NO. 5

Active ingredients

Avobenzone 3 %, Homosalate 7.5 %, Octisalate 5 %, Octocrylene 2.75 %, and Oxybenzone 2 %

Purpose

Sunscreen

Uses

- helps prevent sunburn
- if used as directed with other sun protection measures (see Directions), decreases the risk of skin cancer and early skin aging caused by the sun

Warnings

OTHER SAFETY INFORMATION

For external use only

Do not use on damaged or broken skin.

When using this product keep out of eyes. Rinse with water to remove.

Stop use and ask a doctor if rash occurs.

Keep out of reach of children. If product is swallowed, get medical help or contact a Poison Control Center right away.

OTHER SAFETY INFORMATION

Flammable: Do not use near heat, flame or while smoking.

Directions

- apply liberally and spread evenly by hand 15 minutes before sun exposure
- hold container 4 to 6 inches from the skin to apply
- do not spray directly into face. Spray on hands then apply to face
- do not apply in windy conditions
- use in well-ventilated area
- reapply:
  - after 80 minutes of swimming or sweating
  - immediately after towel drying
  - at least every 2 hours
- Sun Protection Measures. Spending time in the sun increases your risk of skin cancer and early skin aging. To decrease this risk, regularly use a sunscreen with a broad spectrum SPF of 15 or higher and other sun protection measures including:
  - limit time in the sun, especially from 10 a.m. – 2 p.m.
  - wear long-sleeve shirts, pants, hats, and sunglasses
- children under 6 months: Ask a doctor

Inactive Ingredients

Blue 1 (CI 42090), Diethylhexyl 2,6-Naphthalate, Fragrance (Parfum), Glycerin, Polyester-8, Red 40 (CI 16035), SD Alcohol 40-B (Alcohol Denat.), VA/Butyl Maleate/Isobornyl Acrylate Copolymer, Terminalia Ferdinandiana (Kakadu Plum) Fruit Extract, Water (Aqua), Yellow 5 (CI 19140)

Other information

- protect this product from excesive heat and direct sun
- avoid spraying on fabrics - could cause discoloration.

Questions or Comments?

Call toll free 1-855-LIV-GOLD (548-4653)

PRINCIPAL DISPLAY PANEL - 177 mL Bottle Label

EXOTIC BLEND

#1 Fragrance

30

Continuous Spray Sunscreen

with instant

BRONZER

BROAD SPECTRUM SPF 30

WATER RESISTANT (80 MINUTES)

Australian

Gold

6 FL OZ (177 mL)